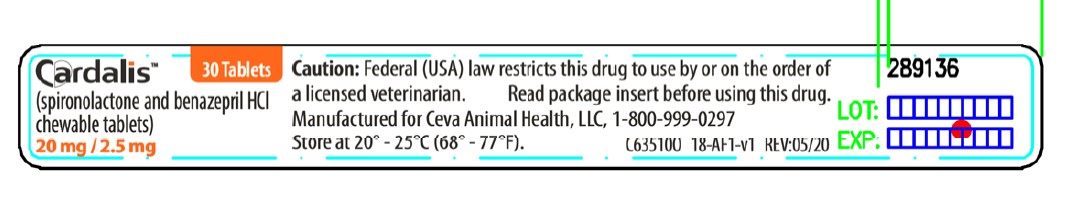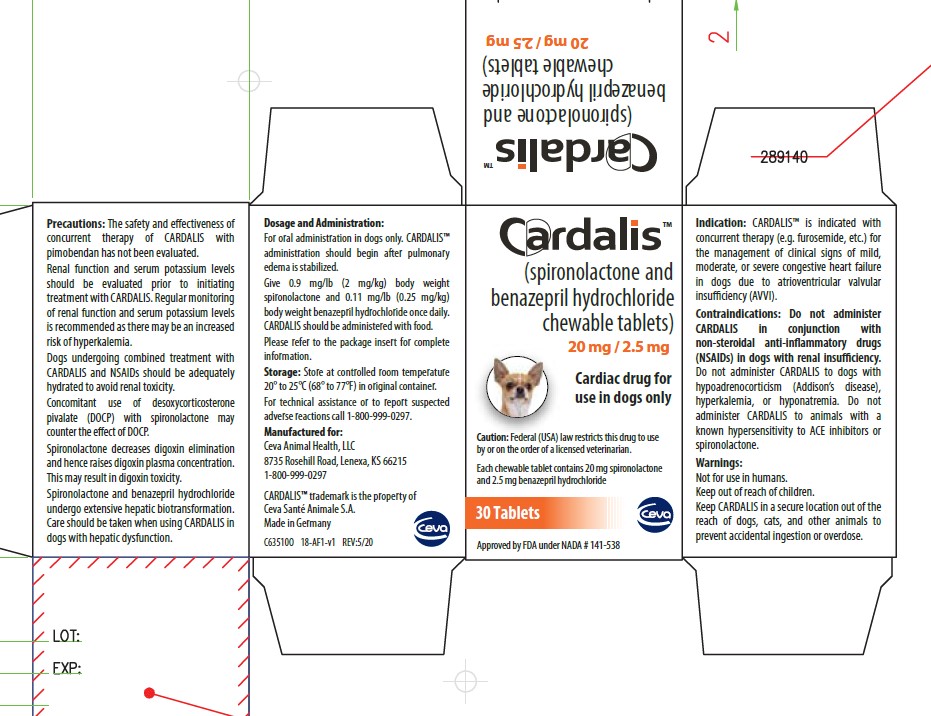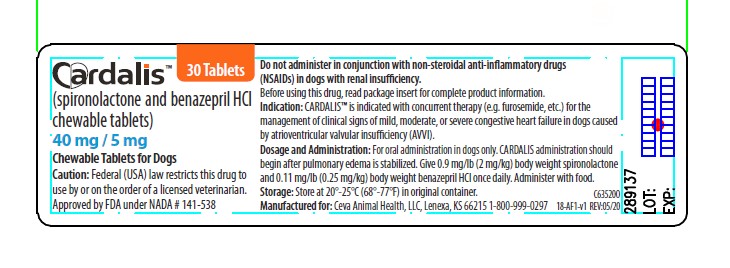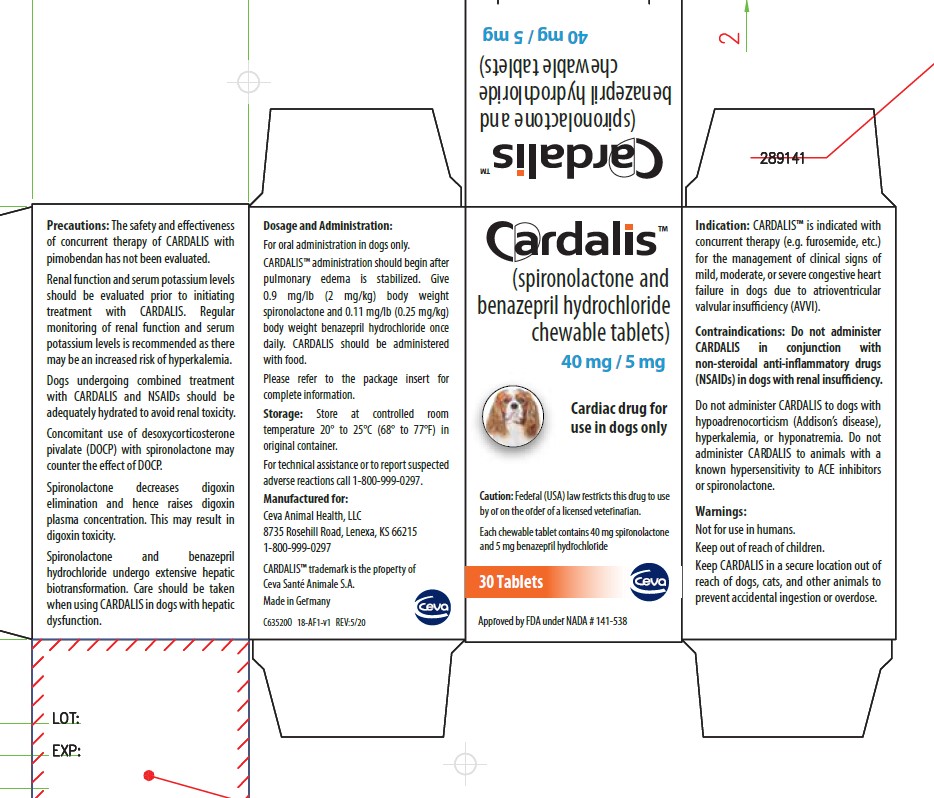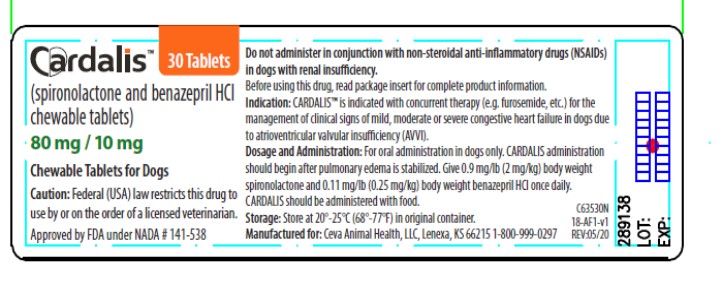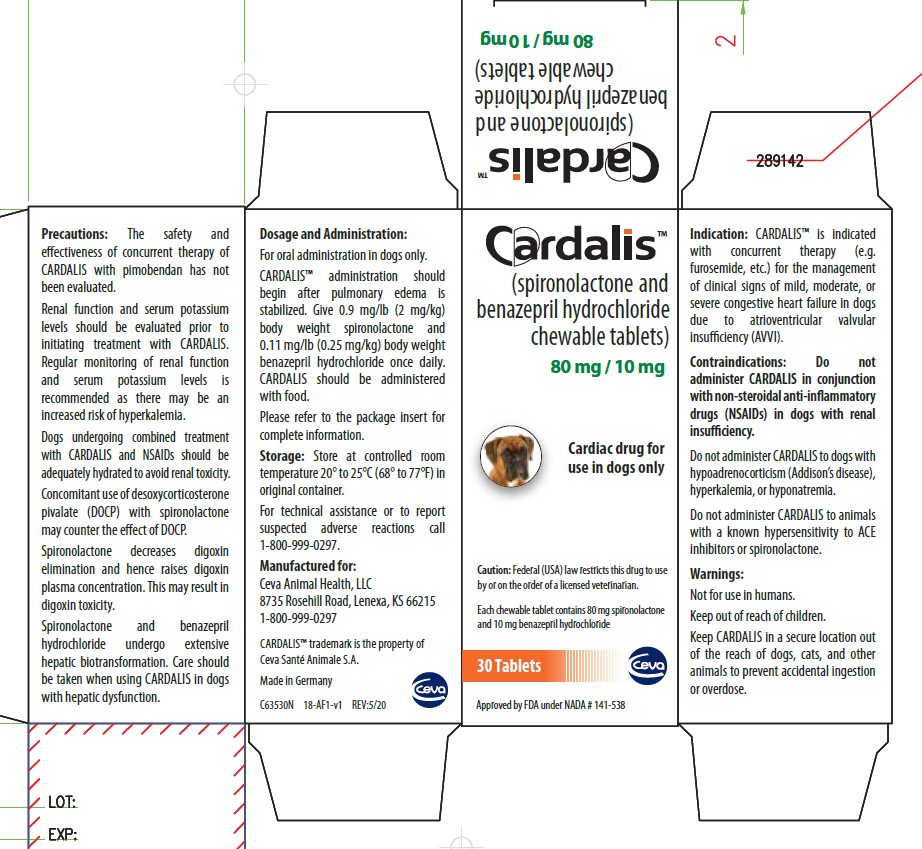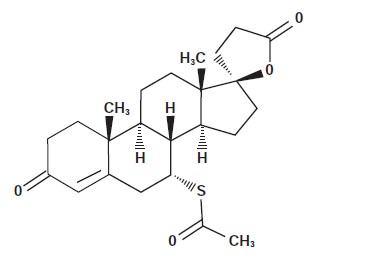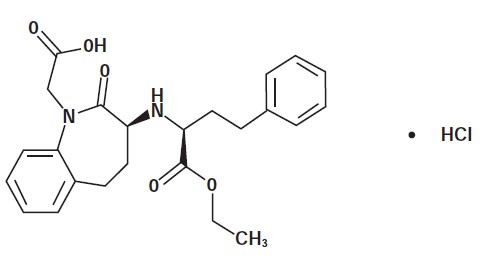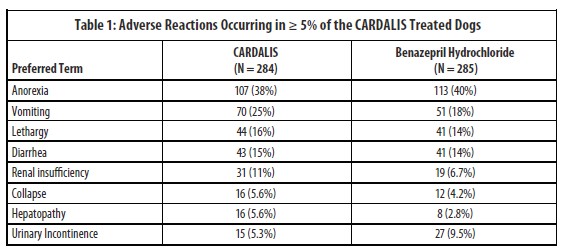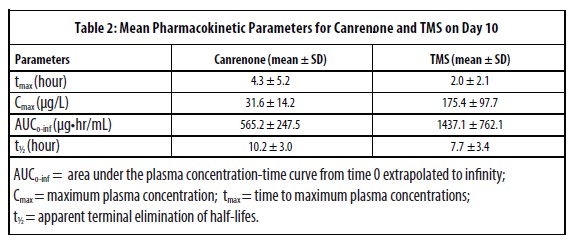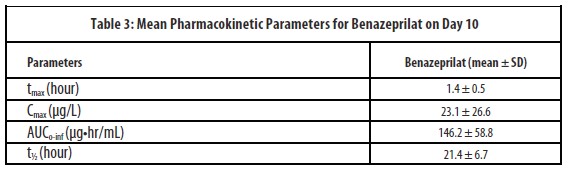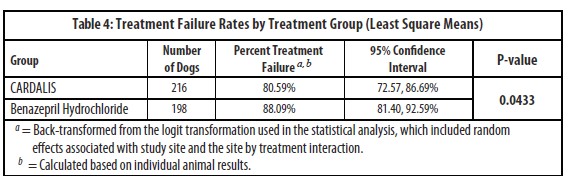 DRUG LABEL: CARDALIS
NDC: 13744-805 | Form: TABLET, CHEWABLE
Manufacturer: Ceva Sante Animale
Category: animal | Type: PRESCRIPTION ANIMAL DRUG LABEL
Date: 20220420

ACTIVE INGREDIENTS: SPIRONOLACTONE 20 mg/1 1; BENAZEPRIL HYDROCHLORIDE 2.5 mg/1 1

Cardalis™

(spironolactone and benazepril hydrochloride chewable tablets)

Cardiac drug for oral use in dogs only

Approved by FDA under NADA # 141-538

Caution: Federal (USA) law restricts this drug to use by or on the order of a licensed veterinarian.

Description:

CARDALIS (spironolactone and benazepril hydrochloride chewable tablets) for dogs contains two active ingredients, spironolactone and benazepril hydrochloride, in a fixed ratio of 8:1 respectively. CARDALIS is supplied as oblong half scored flavored chewable tablets in three sizes:

20 mg spironolactone and 2.5 mg benazepril hydrochloride, 40 mg spironolactone and 5 mg benazepril hydrochloride, and 80 mg spironolactone and 10 mg benazepril hydrochloride.

Benazepril belongs to the angiotensin-converting enzyme (ACE) inhibitor class of drugs. Benazepril hydrochloride empirical formula is C24H28N2O5 · HCl and the molecular weight is 460.95. The chemical name is 3-[[1-(ethoxy-carbonyl)-3-phenyl-(1S)-propyl]amino]-2,3,4,5-tetrahydro-2-oxo-1H-1-(3S)-benazepine-1-acetic acid monohydrochloride and the structural formula is shown below:

Spironolactone, and its active metabolites, act as specific aldosterone antagonists. Spironolactone empirical formula is C24H32O4S and the molecular weight is 416.57. The chemical name is 17-hydroxy-7α-mercapto-3-oxo-17α-pregn-4-ene-21-carboxylic acid y-lactone acetate and the structural formula is shown below:

Indications:

CARDALIS is indicated with concurrent therapy (e.g. furosemide, etc.) for the management of clinical signs of mild, moderate, or severe congestive heart failure in dogs due to atrioventricular valvular insufficiency (AVVI).

Dosage and Administration:

CARDALIS administration should begin after pulmonary edema is stabilized. CARDALIS should be administered orally once daily at a dose of 0.9 mg/lb (2 mg/kg) spironolactone and 0.11 mg/lb (0.25 mg/kg) benazepril hydrochloride, according to dog body weight using a suitable combination of whole and/or half tablets. All tablet strengths are scored and the calculated dosage according to dog’s weight should be to the nearest half-tablet increment. CARDALIS should be administered with food.

Contraindications:

Do not administer CARDALIS in conjunction with non-steroidal anti-inflammatory drugs (NSAIDs) in dogs with renal insufficiency. Do not administer CARDALIS to dogs with hypoadrenocorticism (Addison’s Disease), hyperkalemia, or hyponatremia. Do not administer CARDALIS to animals with known hypersensitivity to ACE inhibitors or spironolactone.

Warnings:

Keep CARDALIS in a secure location out of reach of dogs, cats, and other animals to prevent accidental ingestion or overdose. In case of accidental overdose, induce vomiting, lavage the stomach (depending on risk assessment), and monitor electrolytes. Symptomatic therapy (e.g. fluid therapy) should be provided as medically necessary. CARDALIS is only for use in dogs with clinical evidence of heart failure.

Human Warnings: Not for use in humans. Keep this and all medications out of the reach of children. Consult a physician in case of ingestion by humans.

Precautions:

The safety and effectiveness of concurrent therapy of CARDALIS with pimobendan has not been evaluated.

Renal function and serum potassium levels should be evaluated prior to initiating treatment with CARDALIS. Regular monitoring of renal function and serum potassium levels is recommended as there may be an increased risk of hyperkalemia.

Dogs undergoing combined treatment with CARDALIS and NSAIDs should be adequately hydrated to avoid renal toxicity.

Concomitant use of desoxycorticosterone pivalate (DOCP) with spironolactone may counter the effect of DOCP as DOCP has an opposing mechanism of action to potassium-sparing diuretics like spironolactone. Closely monitor dogs receiving digoxin and spironolactone. Spironolactone decreases digoxin elimination and hence raises digoxin plasma concentration. This may result in digoxin toxicity.

Spironolactone and benazepril hydrochloride undergo extensive hepatic biotransformation. Care should be taken when using CARDALIS in dogs with hepatic dysfunction.

The safety of CARDALIS has not been evaluated in growing dogs. Spironolactone has an antiandrogenic effect and should be used with caution in growing dogs. The safety of CARDALIS has not been established in pregnant, lactating or breeding dogs.

Adverse Reactions:

A U.S. clinical field study comprised of a 360-day treatment period evaluated the safety and effectiveness of CARDALIS compared to benazepril hydrochloride in 569 client-owned dogs with left-sided AVVI. Table 1 summarizes the adverse reactions not directly related to the progression of disease that occurred in greater than 5% of the dogs treated with CARDALIS.

The following adverse events were seen in fewer than 5% of the study animals, in decreasing order: urine abnormalities, fluid in abdomen, ataxia, weight loss, digestive tract disorder, hypertension, electrolyte disorder, bronchitis, and hyperactivity.

Renal insufficiency was reported more frequently in dogs treated with CARDALIS. This finding may be also attributed to the concurrent administration of furosemide. The clinical pathology parameters associated with renal function were not statistically different between the treatment groups.

The incidence of death, including euthanasia and sudden death, was similar in dogs treated with CARDALIS or benazepril hydrochloride. In most cases, death was attributable to the progression of heart disease or the clinical signs associated with congestive heart failure. Deaths of unknown cause were presumed to be cardiac in nature.

Serum magnesium and potassium values were significantly higher in the CARDALIS group, although the mean values remained within the reference range and did not change significantly over time. These electrolyte changes are consistent with the potassium-sparing properties of spironolactone. One dog treated with CARDALIS was removed from the study at Day 7 because it developed hyperkalemia.

Contact Information: To report suspected adverse events or to request a copy of the Safety Data Sheet (SDS), please call Ceva Animal Health at 1-800-999-0297. For additional information about adverse drug experience reporting for animal drugs, contact FDA at 1-888-FDA-VETS or online at www.fda.gov/reportanimalae.

Clinical Pharmacology:

Mechanism of Action: The main pharmacological target of spironolactone and benazepril is the renin-angiotensin-aldosterone system (RAAS) at different levels in the cascade. Spironolactone and its active metabolites (including 7-α-thiomethyl-spironolactone and Canrenone) act as specific antagonists of aldosterone (regardless of the source) by binding competitively to mineralocorticoid receptors located in the kidneys, heart and blood vessels.

Benazepril hydrochloride is a prodrug hydrolyzed in vivo into its active metabolite, benazeprilat. Benazeprilat is a highly potent and selective inhibitor of angiotensin-converting enzyme (ACE), thus preventing the conversion of inactive angiotensin I to active angiotensin II. This prevents deleterious effects of vasoconstriction and aldosterone release, including sodium and water retention, and vascular and myocardial remodeling. However, aldosterone release is not fully controlled by ACE inhibitors because angiotensin II is also produced by non-ACE pathways. Therefore, concomitant use of the aldosterone antagonist spironolactone and the ACE inhibitor benazepril hydrochloride inhibits both ACE and non-ACE pathways.

Pharmacokinetics: Spironolactone is rapidly and extensively metabolized in humans and experimental animals, with species differences in the metabolism and disposition. Spironolactone is metabolized by microsomal cytochrome P450 enzymes to a primary metabolite, canrenone, and a secondary metabolite, 7α-thiomethyl-spironolactone (TMS), which are used as markers for spironolactone in dog plasma. Systemic exposure to both metabolites was comparable when spironolactone was administered alone or in association with benazepril in dogs. Spironolactone absorption is affected by food and the dose should be administered consistently in fed condition. Spironolactone is mainly excreted as metabolites. After oral administration of radiolabeled spironolactone to the dog, 70% of the dose is recovered in feces and 20% in the urine.

After multiple oral doses of 20 mg of spironolactone in association with 2.5 mg of benazepril in dogs (n=18, 9 male and 9 female) for 10 consecutive days (steady state), no accumulation was observed.

Benazepril hydrochloride is a prodrug which, after absorption from the gastrointestinal tract, is rapidly converted by nonspecific carboxyl esterases, mainly in the liver, into its active metabolite benazeprilat. Benazeprilat is itself poorly absorbed from the gastrointestinal tract and the overall bioavailability of benazeprilat after oral administration is estimated to be less than 7%.

After multiple oral doses of 2.5 mg of benazepril in association with 20 mg of spironolactone in dogs (n=18, 9 male and 9 female) for 10 consecutive days (steady state), no accumulation was observed. In dogs, benazeprilat is excreted approximately equally by both renal (45%) and hepatic (55%) routes.

SUMMARY OF SAFETY AND EFFECTIVENESS

Effectiveness: The effectiveness of CARDALIS was evaluated in a well controlled U.S. multi-center, masked, randomized, 360-day field study in client-owned dogs. This study evaluated the effectiveness of CARDALIS in dogs diagnosed with congestive heart failure caused by left-sided AVVI compared to benazepril hydrochloride alone (active control).

Dogs ranged from 3 to 19 years of age and 5 to 155 lbs (2.3 to 70.5 kg) at enrollment. The most common breeds were mixed breed, Cavalier King Charles Spaniel, Chihuahua, Shih Tzu, Maltese, Dachshund, and Yorkshire Terrier. Enrolled dogs demonstrated radiographic evidence of congestive heart failure prior to enrollment or on Day 0 and exhibited clinical signs associated with left-sided AVVI, including exercise intolerance and/or dyspnea, echocardiographic evidence of left-atrial enlargement, moderate-to-severe mitral regurgitation, and presence of a left-sided cardiac murmur. Dogs with acquired heart disease other than left-sided AVVI, congenital heart defect, current positive heartworm antigen test, or syncope not related to heart disease, and dogs intended for breeding or known to be pregnant or lactating, were excluded.

A total of 569 dogs were treated with either CARDALIS (284 dogs) at a dose of 2 mg/kg spironolactone and 0.25 mg/kg benazepril hydrochloride once daily or benazepril hydrochloride alone (285 dogs) at a dose of 0.25 mg/kg once daily. Doses were administered with food or within 30 minutes of feeding. All dogs received concurrent administration of oral furosemide throughout the study (up to 8 mg/kg/day), to manage pulmonary edema. Digoxin and calcium channel blockers were allowed for control of supraventricular arrhythmias. The use of injectable furosemide was permitted during the study evaluation period only if used in place of an equivalent oral dose.

The rate of treatment failure was the primary effectiveness variable used to compare CARDALIS to benazepril hydrochloride alone. Treatment failure was defined as cardiac death or euthanasia (including death of unknown cause), recurrence or worsening of pulmonary edema, newly documented cardiogenic ascites, or clinical signs of congestive heart failure requiring administration of a furosemide dosage higher than 8 mg/kg/day. Failure rates at study Days 30, 90, 180, and 270 were also evaluated as secondary outcomes.

The rate of failure in the CARDALIS group estimated from the model analysis was statistically different (P = 0.0433) and numerically lower than that of the benazepril hydrochloride alone group, as summarized in Table 4.

Further, the rate of failure in the CARDALIS group was significantly lower than the group administered benazepril hydrochloride alone at all evaluation periods past study Day 30. The dogs in the CARDALIS group exhibited a longer median time-to-failure when compared to the control group.

CARDALIS was safely administered in dogs concurrently receiving furosemide, digoxin, calcium channel blockers, antiparasitics, analgesics/anti-inflammatories, antibacterials, routine canine vaccines, respiratory treatments, and gastrointestinal treatments.

Palatability: During the field study, 233 dogs were offered CARDALIS once daily for 14 days. CARDALIS was accepted voluntarily, with or without food, in 87.6% of the 3178 reported doses.

Animal Safety: In a laboratory at safety study, 32 healthy one-year old Beagle dogs (16 males and 16 females) were randomly assigned to an untreated control group or were dosed orally with CARDALIS once daily for 26 weeks at 0, 1X, 3X, and 5X the maximum recommended daily dose (4 mg/kg spironolactone and 0.5 mg/kg benazepril hydrochloride). No dogs were removed and no unscheduled deaths occurred during the study. The dogs dosed with CARDALIS showed no test article-related effects on food or water consumption, body weights, electrocardiographic findings, or blood pressure. The dogs in the 5X group had lower mean heart rates compared to the other groups at the end of the study.

Increased mean serum potassium levels were found in dogs in all CARDALIS dose groups but remained within reference range. There was a dose-related decrease in red cell mass (mean red blood cell count, hemocrit and hemoglobin) but all variables remained within reference ranges. There were decreases in mean prostate weights in the 3X and 5X groups and signs of slight to marked atrophy of prostate glandular tissue. There was a thickening of the zona glomerulosa of adrenal glands in both male and female in the 3X and 5X treated animals.

Systemic exposure to the active metabolites of spironolactone (canrenone and 7-α-thiomethyl-spironolactone) and benazepril (benazeprilat) was shown at the three dose levels throughout the study, with no apparent gender effect. Canrenone and benazeprilat exposures were more than dose proportional at steady-state. There was no accumulation with repeated benazeprilat exposures; canrenone accumulation was 30%. Systemic exposure to 7-α-thiomethyl-spironolactone were variable by study day and dose of spironolactone; steady state, dose proportionality, and accumulation could not be determined.

Storage Information:

Store at controlled room temperature, 20° to 25°C (68° to 77°F), in original container. Excursions permitted between 15°C and 30°C (between 59° and 86°F).

How Supplied:

CARDALIS chewable tablets for dogs are available in 3 sizes of oblong half scored flavored tablets: 20 mg spironolactone and 2.5 mg benazepril hydrochloride, 40 mg spironolactone and 5 mg benazepril hydrochloride, and 80 mg spironolactone and 10mg benazepril hydrochloride. Each size is available in 30-count bottles enclosed in color coded packages.

CARDALIS™ trademark is the property of Ceva Santé Animale S.A.

Made in Germany

Manufactured for:
Ceva Animal Health, LLC
8735 Rosehill Road
Lenexa, KS 66215

PRINCIPAL DISPLAY PANEL - 20/2.5 mg Bottle Label

30 Tablets

Cardalis™

(spironolactone and benazepril hydrochloride chewable tablets)

20 mg/2.5 mg

Caution: Federal (USA) law restricts this drug to use by or on the order of a licensed veterinarian.

Read package insert before using this drug.

Manufactured for Ceva Animal Health, LLC, 1-800-999-0297

Store at 20-25C (68-77F).

PRINCIPAL DISPLAY PANEL - 20/2.5 mg Carton Label

Cardalis™

(spironolactone and benazepril hydrochloride chewable tablets)

20 mg/2.5 mg

Cardiac drug for oral use in dogs only

Caution: Federal (USA) law restricts this drug to use by or on the order of a licensed veterinarian.

Each chewable tablet contains 20 mg spironolactone and 2.5 mg benazepril hydrochloride

30 Tablets

Approved by FDA under NADA # 141-538

PRINCIPAL DISPLAY PANEL - 40/5 mg Bottle Label

30 Tablets

Cardalis™

(spironolactone and benazepril hydrochloride chewable tablets)

40 mg/5 mg

Chewable Tablets for Dogs

Caution: Federal (USA) law restricts this drug to use by or on the order of a licensed veterinarian.

Approved by FDA under NADA # 141-538

PRINCIPAL DISPLAY PANEL - 40/5 mg Carton Label

Cardalis™

(spironolactone and benazepril hydrochloride chewable tablets)

40 mg/5 mg

Cardiac drug for oral use in dogs only

Caution: Federal (USA) law restricts this drug to use by or on the order of a licensed veterinarian.

Each chewable tablet contains 20 mg spironolactone and 2.5 mg benazepril hydrochloride

30 Tablets

Approved by FDA under NADA # 141-538

PRINCIPAL DISPLAY PANEL - 80/10 mg Carton Label

30 Tablets

Cardalis™

(spironolactone and benazepril hydrochloride chewable tablets)

80 mg/10 mg

Chewable Tablets for Dogs

Caution: Federal (USA) law restricts this drug to use by or on the order of a licensed veterinarian.

Approved by FDA under NADA # 141-538

PRINCIPAL DISPLAY PANEL - 80/10 mg Carton Label

Cardalis™

(spironolactone and benazepril hydrochloride chewable tablets)

80 mg/10 mg

Cardiac drug for oral use in dogs only

Caution: Federal (USA) law restricts this drug to use by or on the order of a licensed veterinarian.

Each chewable tablet contains 20 mg spironolactone and 2.5 mg benazepril hydrochloride

30 Tablets

Approved by FDA under NADA # 141-538